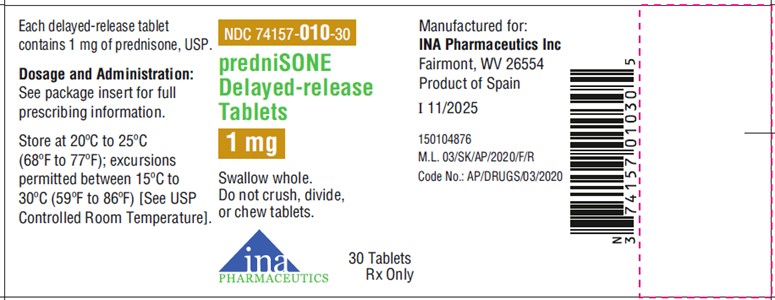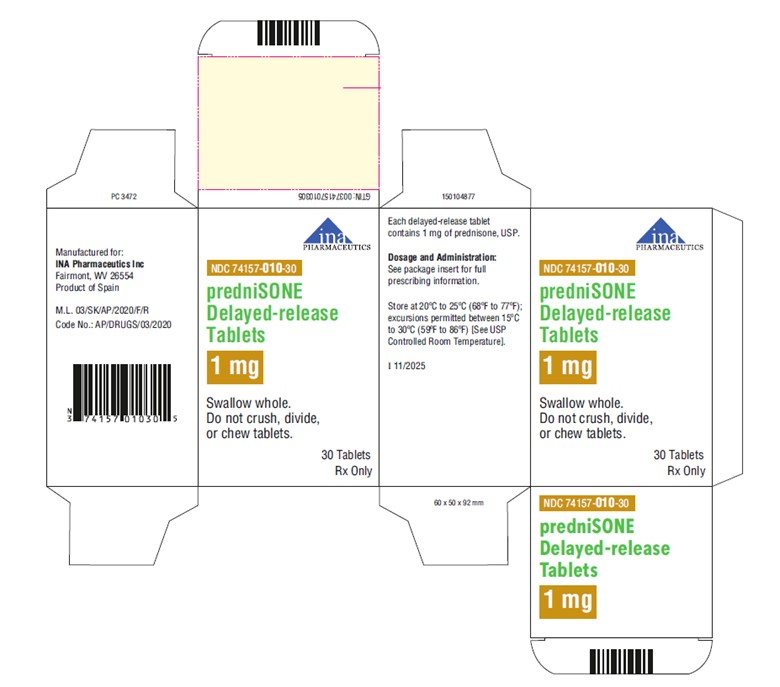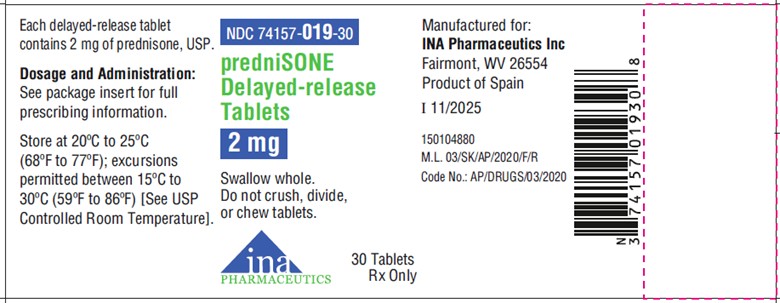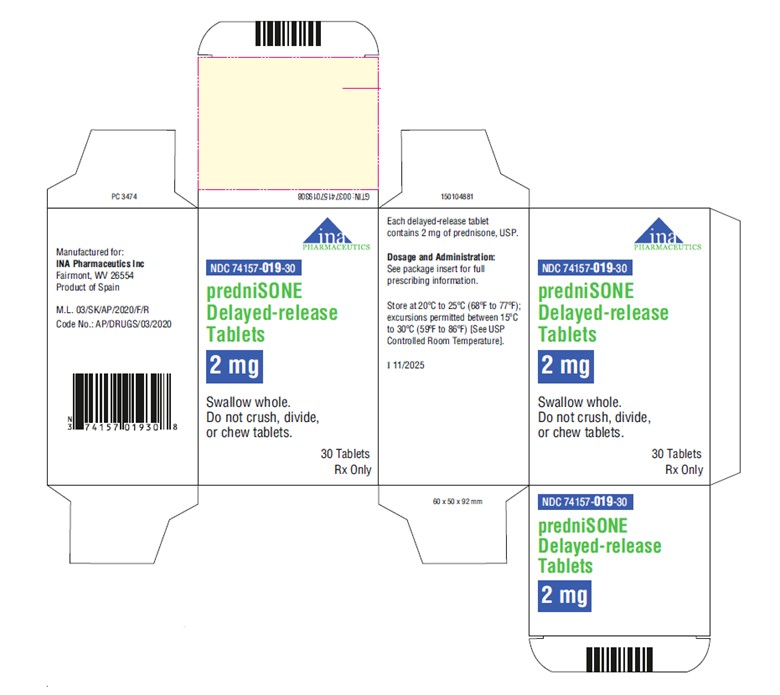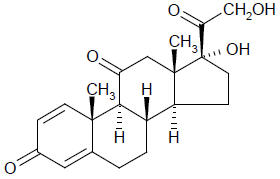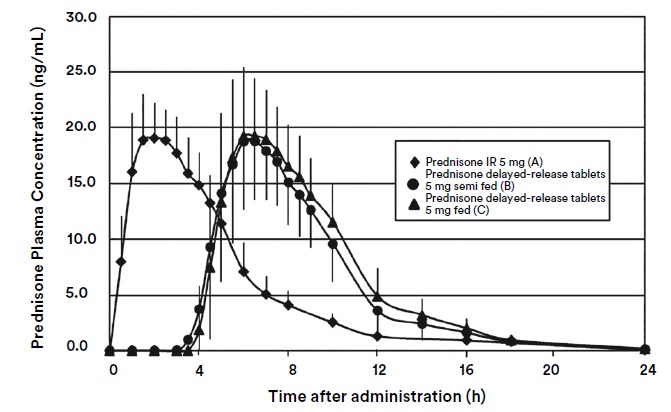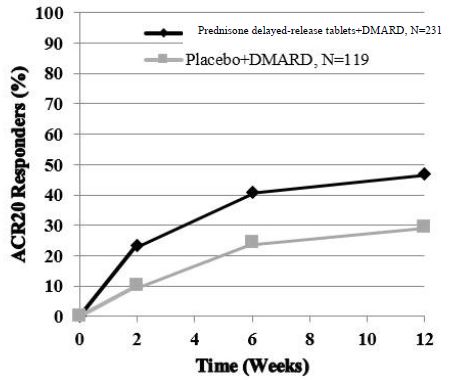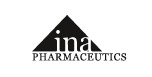 DRUG LABEL: Prednisone delayed release
NDC: 74157-010 | Form: TABLET, DELAYED RELEASE
Manufacturer: INA Pharmaceutics Inc
Category: prescription | Type: HUMAN PRESCRIPTION DRUG LABEL
Date: 20251217

ACTIVE INGREDIENTS: PREDNISONE 1 mg/1 1
INACTIVE INGREDIENTS: LACTOSE MONOHYDRATE; POVIDONE, UNSPECIFIED; CROSCARMELLOSE SODIUM; SILICON DIOXIDE; MAGNESIUM STEARATE; FERRIC OXIDE RED; GLYCERYL DIBEHENATE; WATER; FERRIC OXIDE YELLOW

HIGHLIGHTS OF PRESCRIBING INFORMATION

These highlights do not include all the information needed to use PREDNISONE DELAYED-RELEASE TABLETS safely and effectively. See full prescribing information for PREDNISONE DELAYED-RELEASE TABLETS.
PREDNISONE delayed-release tablets, for oral use
Initial U.S. Approval: 1955

RECENT MAJOR CHANGES

Warnings and Precautions, Immunosuppressionand Increased Risk of Infection (5.2) 03/2024

1 INDICATIONS AND USAGE

Prednisone delayed-release tablets are a corticosteroid indicated

- as an anti-inflammatory or immunosuppressive agent for certain allergic, dermatologic, gastrointestinal, hematologic, ophthalmologic, nervous system, renal, respiratory, rheumatologic, specific infectious diseases or conditions and organ transplantation (1)
- for the treatment of certain endocrine conditions (1)
- for palliation of certain neoplastic conditions (1)

2 DOSAGE AND ADMINISTRATION

Individualize dosing based on disease severity and patient response. The timing of administration should take into account the delayed-release pharmacokinetics and the disease or condition being treated (2, 12.1):

- Initial dose: Prednisone delayed-release tablets 5 mg administered once per day. Patients currently on immediate-release prednisone, prednisolone, or methylprednisolone should be switched to prednisone delayed-release tablets at an equivalent dose based on relative potency. (2.1, 2.4)
- Maintenance dose: Use lowest dosage that will maintain an adequate clinical response. (2.1)
- Discontinuation: Withdraw gradually if discontinuing long-term or high-dose therapy. (2.1)
- Prednisone delayed-release tablets should be taken daily with food. (2.3, 12.3)
- Prednisone delayed-release tablets should be swallowed whole and not broken, divided, or chewed. (2.3)

3 DOSAGE FORMS AND STRENGTHS

- Delayed-release tablets: 1 mg, and 2 mg prednisone (3)

4 CONTRAINDICATIONS

- Known hypersensitivity to prednisone or any excipients in the formulation (4, 6)

5 WARNINGS AND PRECAUTIONS

- Hypothalamic-pituitary-adrenal (HPA) axis suppression, Cushing's syndrome, and hyperglycemia: Monitor patients for these conditions with chronic use. Taper doses gradually for withdrawal after chronic use. (5.1)
- Immunosuppression and Increased Risk of Infection: Increased susceptibility to new infection and increased risk of exacerbation, dissemination, or reactivation of latent infection. Signs and symptoms of infection may be masked. (5.2)
- Elevated blood pressure, salt and water retention, and hypokalemia: Monitor blood pressure and sodium, potassium serum levels (5.3)
- GI perforation: increased risk in patients with certain GI disorders. Signs and symptoms may be masked. (5.4)
- Behavioral and mood disturbances: May include euphoria, insomnia, mood swings, personality changes, severe depression, and psychosis. Existing conditions may be aggravated. (5.5)
- Decreases in bone density: Monitor bone density in patients receiving long term corticosteroid therapy. (5.6)
- Ophthalmic effects: May include cataracts, infections, and glaucoma. Monitor intraocular pressure if corticosteroid therapy is continued for more than 6 weeks (5.7)
- Live or live attenuated vaccines: Do not administer to patients receiving immunosuppressive doses of corticosteroids. (5.8)
- Negative effects on growth and development: Monitor pediatric patients on long-term corticosteroid therapy. (5.9)
- Embryo-Fetal Toxicity: Can cause fetal harm with first trimester use. Advise patients of potential harm to the fetus. (5.10)

6 ADVERSE REACTIONS

Common adverse reactions for corticosteroids include fluid retention, alteration in glucose tolerance, elevation in blood pressure, behavioral and mood changes, increased appetite and weight gain. (6)

To report SUSPECTED ADVERSE REACTIONS, contact INA Pharmaceutics Inc at 1-866-835-0469 or FDA at 1-800-FDA-1088 or www.fda.gov/medwatch.

7 DRUG INTERACTIONS

- Anticoagulant agents: May enhance or diminish anticoagulant effects. (7.4)
- Antidiabetic agents: May increase blood glucose concentrations. Dose adjustments of antidiabetic agents may be required. (7.5)
- CYP 3A4 inducers and inhibitors: May, respectively, increase or decrease clearance of corticosteroids, necessitating dose adjustment. (7.7, 7.8)
- Cyclosporine: Increase in activity of both, cyclosporine and corticosteroid when administered concurrently. Convulsions have been reported with concurrent use. (7.10)
- NSAIDs including aspirin and salicylates: Increased risk of gastrointestinal side effects. (7.13)

FULL PRESCRIBING INFORMATION

1 INDICATIONS AND USAGE

Prednisone delayed-release tablets are indicated in the treatment of the following diseases or conditions:

1.1 Allergic Conditions

Control of severe or incapacitating allergic conditions intractable to adequate trials of conventional treatment in adults and pediatric populations with:

- Atopic dermatitis
- Drug hypersensitivity reactions
- Seasonal or perennial allergic rhinitis
- Serum sickness

1.2 Dermatologic Diseases

- Bullous dermatitis herpetiformis
- Contact dermatitis
- Exfoliative erythroderma
- Mycosis fungoides
- Pemphigus
- Severe erythema multiforme (Stevens-Johnson syndrome)

1.3 Endocrine Conditions

- Congenital adrenal hyperplasia
- Hypercalcemia of malignancy
- Nonsuppurative thyroiditis
- Primary or secondary adrenocortical insufficiency: hydrocortisone or cortisone is the first choice: synthetic analogs may be used in conjunction with mineralocorticoids where applicable

1.4 Gastrointestinal Diseases

During acute episodes in:

- Crohn's Disease
- Ulcerative colitis

1.5 Hematologic Diseases

- Acquired (autoimmune) hemolytic anemia
- Diamond-Blackfan anemia
- Idiopathic thrombocytopenic purpura in adults
- Pure red cell aplasia
- Secondary thrombocytopenia in adults

1.6 Neoplastic Conditions

For the treatment of:

- Acute leukemia
- Aggressive lymphomas

1.7 Nervous System Conditions

- Acute exacerbations of multiple sclerosis
- Cerebral edema associated with primary or metastatic brain tumor, craniotomy or head injury

1.8 Ophthalmic Conditions

- Sympathetic ophthalmia
- Uveitis and ocular inflammatory conditions unresponsive to topical steroids

1.9 Conditions Related to Organ Transplantation

- Acute or chronic solid organ rejection

1.10 Pulmonary Diseases

- Acute exacerbations of chronic obstructive pulmonary disease (COPD)
- Allergic bronchopulmonary aspergillosis
- Aspiration pneumonitis
- Asthma
- Fulminating or disseminated pulmonary tuberculosis when used concurrently with appropriate chemotherapy
- Hypersensitivity pneumonitis
- Idiopathic bronchiolitis obliterans with organizing pneumonia
- Idiopathic eosinophilic pneumonias
- Idiopathic pulmonary fibrosis
- Pneumocystis carinii pneumonia (PCP) associated with hypoxemia occurring in an HIV(+) individual who is also under treatment with appropriate anti-PCP antibiotics.
- Symptomatic sarcoidosis

1.11 Renal Conditions

- To induce a diuresis or remission of proteinuria in nephrotic syndrome, without uremia, of the idiopathic type or that due to lupus erythematosus

1.12 Rheumatologic Conditions

As adjunctive therapy for short-term administration (to tide the patient over an acute episode or exacerbation) in:

- Acute gouty arthritis

During an exacerbation or as maintenance therapy in selected cases of:

- Ankylosing spondylitis
- Dermatomyositis/polymyositis
- Polymyalgia rheumatica
- Psoriatic arthritis
- Relapsing polychondritis
- Rheumatoid arthritis, including juvenile rheumatoid arthritis (selected cases may require low dose maintenance therapy)
- Sjogren's syndrome
- Systemic lupus erythematosus
- Vasculitis

1.13 Specific Infectious Diseases

- Trichinosis with neurologic or myocardial involvement.
- Tuberculous meningitis with subarachnoid block or impending block used concurrently with appropriate antituberculous chemotherapy.

2 DOSAGE AND ADMINISTRATION

2.1 Recommended Dosing

Dosage of prednisone delayed-release tablets should be individualized according to the severity of the disease and the response of the patient. For pediatric patients, the recommended dosage should be governed by the same considerations rather than strict adherence to the ratio indicated by age or body weight.

The maximal activity of the adrenal cortex is between 2 am and 8 am and is minimal between 4 pm and midnight. Exogenous corticosteroids suppress adrenocorticoid activity the least when given at the time of maximal activity. Prednisone delayed-release tablet is a delayed-release formulation of prednisone which releases the active substance beginning approximately 4 hours after intake [ see Clinical Pharmacology (12.3)]. The timing of prednisone delayed-release tablets administration should take into account the delayed-release pharmacokinetics and the disease or condition being treated.

The initial dosage of prednisone delayed-release tablets may vary from 5 to 60 mg per day depending on the specific disease entity being treated. Patients currently on immediate release prednisone, prednisolone, or methylprednisolone should be switched to prednisone delayed-release tablets at an equivalent dose based on relative potency (2.4).

In situations of less severity, lower doses will generally suffice while in selected patients higher initial doses may be required. The initial dosage should be maintained or adjusted until a satisfactory response is noted. If after a reasonable period there is a lack of satisfactory clinical response, prednisone delayed-release tablets should be discontinued and the patient transferred to other appropriate therapy. It should be emphasized that dosage requirements are variable and must be individualized on the basis of the disease under treatment and the response of the patient.

After a favorable response is noted, the proper maintenance dosage should be determined by decreasing the initial drug dosage in small decrements at appropriate time intervals until the lowest dosage which will maintain an adequate clinical response is reached. It should be kept in mind that constant monitoring is needed in regard to drug dosage. Included in the situations which may make dosage adjustments necessary are changes in clinical status secondary to remissions or exacerbations in the disease process, the patient's individual drug responsiveness, and the effect of patient exposure to stressful situations not directly related to the disease entity under treatment. In this latter situation it may be necessary to increase the dosage of prednisone delayed-release tablets for a period of time consistent with the patient's condition. If a period of spontaneous remission occurs in a chronic condition, treatment should be discontinued. If after long-term therapy the drug is to be stopped, it is recommended that it be withdrawn gradually rather than abruptly.

2.2 Recommended Monitoring

Blood pressure, body weight, routine laboratory studies (including 2-hour postprandial blood glucose and serum potassium), and chest X-ray should be obtained at regular intervals during prolonged therapy with prednisone delayed-release tablets. Upper GI X-rays are desirable in patients with known or suspected peptic ulcer disease.

2.3 Method of Administration

Prednisone delayed-release tablets are for oral administration.

Prednisone delayed-release tablets should be taken daily with food. [see Clinical Pharmacology (12.3)]

Prednisone delayed-release tablets should not be broken, divided, or chewed because the delayed release of prednisone is dependent on an intact coating [see Description (11)].

2.4 Corticosteroid Comparison Chart

For the purpose of comparison, one 5 mg prednisone delayed-release tablet is the equivalent milligram dosage of the following various corticosteroids:

Betamethasone, 0.75 mg | Paramethasone, 2 mg
Cortisone, 25 mg | Prednisolone, 5 mg
Dexamethasone, 0.75 mg | Prednisone, 5 mg
Hydrocortisone, 20 mg | Triamcinolone, 4 mg
Methylprednisolone, 4 mg

These dose relationships apply only to oral or intravenous administration of these compounds. When these substances or their derivatives are injected intramuscularly or into joint spaces, their relative properties may be greatly altered.

3 DOSAGE FORMS AND STRENGTHS

Delayed-release Tablets

- Prednisone delayed release tablets, 1 mg: White to off-white colored, round, unscored, delayed release tablet, debossed with "1" on one side and plain on other side, mottled appearance, free from physical defects.
- Prednisone delayed release tablets, 2 mg: Light peach to peach colored, round, unscored, delayed release tablet, debossed with "2" on one side and plain on other side, mottled appearance, free from physical defects.

4 CONTRAINDICATIONS

Prednisone delayed-release tablets are contraindicated in patients who have known hypersensitivity to prednisone or to any of the excipients. Rare instances of anaphylaxis have occurred in patients receiving corticosteroid therapy [ see Adverse Reactions (6)].

5 WARNINGS AND PRECAUTIONS

5.1 Alterations in Endocrine Function

Hypothalamic-pituitary-adrenal (HPA) axis suppression, Cushing's syndrome, and hyperglycemia. Monitor patients for these conditions with chronic use.

Corticosteroids can produce reversible hypothalamic-pituitary adrenal (HPA) axis suppression with the potential for corticosteroid insufficiency after withdrawal of treatment. Drug-induced secondary adrenocortical insufficiency may be minimized by gradual reduction of dosage. This type of relative insufficiency may persist for months after discontinuation of therapy; therefore, in any situation of stress occurring during that period, hormone therapy should be reinstituted. If the patient is receiving corticosteroids already, dosage may have to be increased.

Since mineralocorticoid secretion may be impaired, salt and/or a mineralocorticoid should be administered concurrently. Mineralocorticoid supplementation is of particular importance in infancy.

Metabolic clearance of corticosteroids is decreased in hypothyroid patients and increased in hyperthyroid patients. Changes in thyroid status of the patient may necessitate adjustment in dosage.

5.2 Immunosuppression and Increased Risk of Infection

Corticosteroids, including prednisone delayed-release tablets, suppress the immune system and increase the risk of infection with any pathogen, including viral, bacterial, fungal, protozoan, or helminthic pathogens. Corticosteroids can:

- Reduce resistance to new infections
- Exacerbate existing infections
- Increase the risk of disseminated infections
- Increase the risk of reactivation or exacerbation of latent infections
- Mask some signs of infection

Corticosteroid-associated infections can be mild but can be severe and at times fatal. The rate of infectious complications increases with increasing corticosteroid dosages.

Monitor for the development of infection and consider prednisone delayed-release tablets withdrawal or dosage reduction as needed.

Tuberculosis

If prednisone delayed-release tablets are used to treat a condition in patients with latent tuberculosis or tuberculin reactivity, reactivation of tuberculosis may occur. Closely monitor such patients for reactivation. During prolonged prednisone delayed-release tablets therapy, patients with latent tuberculosis or tuberculin reactivity should receive chemoprophylaxis.

Varicella Zoster and Measles Viral Infections

Varicella and measles can have a serious or even fatal course in non-immune patients taking corticosteroids, including prednisone delayed-release tablets. In corticosteroid-treated patients who have not had these diseases or are non-immune, particular care should be taken to avoid exposure to varicella and measles:

- If a prednisone delayed-release tablets-treated patient is exposed to varicella, prophylaxis with varicella zoster immune globulin may be indicated. If varicella develops, treatment with antiviral agents may be considered.
- If a prednisone delayed-release tablets-treated patient is exposed to measles, prophylaxis with immunoglobulin may be indicated.

Hepatitis B Virus Reactivation

Hepatitis B virus reactivation can occur in patients who are hepatitis B carriers treated with immunosuppressive dosages of corticosteroids, including prednisone delayed-release tablets. Reactivation can also occur infrequently in corticosteroid-treated patients who appear to have resolved hepatitis B infection.

Screen patients for hepatitis B infection before initiating immunosuppressive (e.g., prolonged) treatment with prednisone delayed-release tablets. For patients who show evidence of hepatitis B infection, recommend consultation with physicians with expertise in managing hepatitis B regarding monitoring and consideration for hepatitis B antiviral therapy.

Fungal Infections

Corticosteroids, including prednisone delayed-release tablets, may exacerbate systemic fungal infections; therefore, avoid prednisone delayed-release tablets use in the presence of such infections unless prednisone delayed-release tablets are needed to control drug reactions. For patients on chronic prednisone delayed-release tablets therapy who develop systemic fungal infections, prednisone delayed-release tablets withdrawal or dosage reduction is recommended.

Amebiasis

Corticosteroids, including prednisone delayed-release tablets, may activate latent amebiasis. Therefore, it is recommended that latent amebiasis or active amebiasis be ruled out before initiating prednisone delayed-release tablets in patients who have spent time in the tropics or patients with unexplained diarrhea.

Strongyloides Infestation

Corticosteroids, including prednisone delayed-release tablets, should be used with great care in patients with known or suspected Strongyloides (threadworm) infestation. In such patients, corticosteroid-induced immunosuppression may lead to Strongyloides hyperinfection and dissemination with widespread larval migration, often accompanied by severe enterocolitis and potentially fatal gram-negative septicemia.

Cerebral Malaria

Avoid corticosteroids, including prednisone delayed-release tablets, in patients with cerebral malaria.

5.3 Alterations in Cardiovascular/Renal Function

Corticosteroids can cause elevation of blood pressure, salt, and water retention, and increased excretion of potassium and calcium. These effects are less likely to occur with the synthetic derivatives except when used in large doses. Dietary salt restriction and potassium supplementation may be necessary. These agents should be used with caution in patients with congestive heart failure, hypertension, or renal insufficiency.

Literature reports suggest an apparent association between use of corticosteroids and left ventricular free wall rupture after a recent myocardial infarction; therefore, therapy with corticosteroids should be used with great caution in these patients.

5.4 Use in Patients with Gastrointestinal Disorders

There is an increased risk of gastrointestinal perforation in patients with certain GI disorders. Signs of GI perforation, such as peritoneal irritation may be masked in patients receiving corticosteroids.

Corticosteroids should be used with caution if there is a probability of impending perforation, abscess, or other pyogenic infections; diverticulitis; fresh intestinal anastomoses; and active or latent peptic ulcer.

5.5 Behavioral and Mood Disturbances

Corticosteroids use may be associated with central nervous system effects ranging from euphoria, insomnia, mood swings, personality changes, and severe depression, to frank psychotic manifestations. Also, existing emotional instability or psychotic tendencies may be aggravated by corticosteroids.

5.6 Decrease in Bone Density

Corticosteroids decrease bone formation and increase bone resorption both through their effect on calcium regulation (i.e., decreasing absorption and increasing excretion) and inhibition of osteoblast function. This, together with a decrease in the protein matrix of the bone secondary to an increase in protein catabolism, and reduced sex hormone production, may lead to inhibition of bone growth in children and adolescents and the development of osteoporosis at any age. Special consideration should be given to patients at increased risk of osteoporosis (i.e., postmenopausal women) before initiating corticosteroid therapy and bone density should be monitored in patients on long term corticosteroid therapy.

5.7 Ophthalmic Effects

Prolonged use of corticosteroids may produce posterior subcapsular cataracts, glaucoma with possible damage to the optic nerves, and may enhance the establishment of secondary ocular infections due to fungi or viruses.

The use of oral corticosteroids is not recommended in the treatment of optic neuritis and may lead to an increase in the risk of new episodes.

Intraocular pressure may become elevated in some individuals. If corticosteroid therapy is continued for more than 6 weeks, intraocular pressure should be monitored.

Corticosteroids should be used cautiously in patients with ocular herpes simplex because of possible corneal perforation. Corticosteroids should not be used in active ocular herpes simplex.

5.8 Vaccination

Administration of live or live, attenuated vaccines is contraindicated in patients receiving immunosuppressive doses of corticosteroids. Killed or inactivated vaccines may be administered; however, the response to such vaccines cannot be predicted. Immunization procedures may be undertaken in patients who are receiving corticosteroids as replacement therapy, e.g., for Addison's disease.

While on corticosteroid therapy, patients should not be vaccinated against smallpox. Other immunization procedures should not be undertaken in patients who are on corticosteroids, especially on high dose, because of possible hazards of neurological complications and a lack of antibody response.

5.9 Effect on Growth and Development

Long-term use of corticosteroids can have negative effects on growth and development in children.

Growth and development of pediatric patients on prolonged corticosteroid therapy should be carefully monitored.

5.10 Embryo-Fetal Toxicity

Prednisone can cause fetal harm when administered to a pregnant woman. Human studies suggest a small but inconsistent increased risk of orofacial clefts with use of corticosteroids during the first trimester of pregnancy. Published animal studies show prednisolone to be teratogenic in rats, rabbits, hamsters, and mice with increased incidence of cleft palate in offspring. Intrauterine growth restriction and decreased birth weight have also been reported with corticosteroid use during pregnancy, however, the underlying maternal condition may also contribute to these risks. If this drug is used during pregnancy, or if the patient becomes pregnant while using this drug, advise the patient about the potential harm to the fetus [see Use in Specific Populations (8.1)].

5.11 Neuromuscular Effects

Although controlled clinical trials have shown corticosteroids to be effective in speeding the resolution of acute exacerbations of multiple sclerosis, they do not show that they affect the ultimate outcome or natural history of the disease. The studies do show that relatively high doses of corticosteroids are necessary to demonstrate a significant effect.

An acute myopathy has been observed with the use of high doses of corticosteroids, most often occurring in patients with disorders of neuromuscular transmission (e.g., myasthenia gravis), or in patients receiving concomitant therapy with neuromuscular blocking drugs (e.g., pancuronium). This acute myopathy is generalized, may involve ocular and respiratory muscles, and may result in quadriparesis. Elevation of creatine kinase may occur. Clinical improvement or recovery after stopping corticosteroids may require weeks to years.

5.12 Kaposi's Sarcoma

Kaposi's sarcoma has been reported to occur in patients receiving corticosteroid therapy, most often for chronic conditions. Discontinuation of corticosteroids may result in clinical improvement of Kaposi’s sarcoma.

6 ADVERSE REACTIONS

Common adverse reactions for corticosteroids include fluid retention, alteration in glucose tolerance, elevation in blood pressure, behavioral and mood changes, increased appetite and weight gain.

Allergic Reactions:Anaphylaxis, angioedema

Cardiovascular:Bradycardia, cardiac arrest, cardiac arrhythmias, cardiac enlargement, circulatory collapse, congestive heart failure, fat embolism, hypertension, hypertrophic cardiomyopathy in premature infants, myocardial rupture following recent myocardial infarction, pulmonary edema, syncope, tachycardia, thromboembolism, thrombophlebitis, vasculitis

Dermatologic:Acne, allergic dermatitis, cutaneous and subcutaneous atrophy, dry scalp, edema, facial erythema, hyper or hypopigmentation, impaired wound healing, increased sweating, petechiae and ecchymoses, rash, sterile abscess, striae, suppressed reactions to skin tests, thin fragile skin, thinning scalp hair, urticaria

Endocrine:Abnormal fat deposits, decreased carbohydrate tolerance, development of Cushingoid state, hirsutism, manifestations of latent diabetes mellitus and increased requirements for insulin or oral hypoglycemic agents in diabetics, menstrual irregularities, moon facies, secondary adrenocortical and pituitary unresponsiveness (particularly in times of stress, as in trauma, surgery or illness), suppression of growth in children

Fluid and Electrolyte Disturbances:Fluid retention, potassium loss, hypertension, hypokalemic alkalosis, sodium retention

Gastrointestinal:Abdominal distention, elevation in serum liver enzymes levels (usually reversible upon discontinuation), hepatomegaly, hiccups, malaise, nausea, pancreatitis, peptic ulcer with possible perforation and hemorrhage, ulcerative esophagitis

General:Increased appetite and weight gain

Metabolic:Negative nitrogen balance due to protein catabolism

Musculoskeletal:Osteonecrosis of femoral and humeral heads, charcot-like arthropathy, loss of muscle mass, muscle weakness, osteoporosis, pathologic fracture of long bones, steroid myopathy, tendon rupture, vertebral compression fractures

Neurological:Arachnoiditis, convulsions, depression, emotional instability, euphoria, headache, increased intracranial pressure with papilledema (pseudo-tumor cerebri) usually following discontinuation of treatment, insomnia, meningitis, mood swings, neuritis, neuropathy, paraparesis/paraplegia, paresthesia, personality changes, sensory disturbances, vertigo

Ophthalmic:Exophthalmos, glaucoma, increased intraocular pressure, posterior subcapsular cataracts, and central serous chorioretinopathy

Reproductive:Alteration in motility and number of spermatozoa

6.1 Clinical Trials Experience

Because clinical trials are conducted under widely varying conditions, adverse reaction rates observed in the clinical trials of a drug cannot be directly compared to rates in the clinical trials of another drug and may not reflect the rates observed in practice.

The safety of prednisone delayed-release tablets was evaluated in 375 rheumatoid arthritis patients in two controlled trials. Patients treated with prednisone delayed-release tablets ranged in age from 20 to 80 years (median age 56 years), with 85% female, 99% Caucasian, 1% African-American, and < 1% Asian.

Patients received prednisone delayed-release tablets 3 mg to 10 mg once daily at 10 pm; the majority (84%) received ≤ 5 mg. The clinical trial experience did not raise new safety concerns beyond those already established for immediate-release prednisone.

6.2 Postmarketing Experience

Adverse reactions have been identified during post approval use of prednisone delayed-release tablets. Because these reactions are reported voluntarily from a population of uncertain size, it is not always possible to reliably estimate their frequency or establish a causal relationship to drug exposure. The postmarketing experience has not raised new safety concerns beyond those already established for immediate-release prednisone.

7 DRUG INTERACTIONS

7.1 Aminoglutethimide

Aminoglutethimide may lead to loss of corticosteroid-induced adrenal suppression.

7.2 Amphotericin B Injection

There have been cases reported in which concomitant use of Amphotericin B and hydrocortisone was followed by cardiac enlargement and congestive heart failure [see Drug Interactions (7.14)] .

7.3 Anticholinesterase Agents

Concomitant use of anticholinesterase agents and corticosteroids may produce severe weakness in patients with myasthenia gravis. If possible, anticholinesterase agents should be withdrawn at least 24 hours before initiating corticosteroid therapy.

7.4 Anticoagulant Agents

Co-administration of corticosteroids and warfarin usually results in inhibition of response to warfarin, although there have been some conflicting reports. Therefore, coagulation indices should be monitored frequently to maintain the desired anticoagulant effect.

7.5 Antidiabetic Agents

Because corticosteroids may increase blood glucose concentrations, dosage adjustments of antidiabetic agents may be required.

7.6 Antitubercular Drugs

Serum concentrations of isoniazid may be decreased.

7.7 CYP 3A4 Inducers (e.g., Barbiturates, Phenytoin, Carbamazepine, and Rifampin)

Drugs such as barbiturates, phenytoin, ephedrine, and rifampin, which induce hepatic microsomal drug metabolizing enzyme activity may enhance the metabolism of corticosteroids and require that the dosage of the corticosteroid be increased.

7.8 CYP 3A4 Inhibitors (e.g., Ketoconazole, Macrolide Antibiotics)

Ketoconazole has been reported to decrease the metabolism of certain corticosteroids by up to 60% leading to increased risk of corticosteroid side effects.

7.9 Cholestyramine

Cholestyramine may increase the clearance of corticosteroids.

7.10 Cyclosporine

Increased activity of both cyclosporine and corticosteroids may occur when the two are used concurrently. Convulsions have been reported with this concurrent use.

7.11 Digitalis

Patients on digitalis glycosides may be at increased risk of arrhythmias due to hypokalemia.

7.12 Estrogens, Including Oral Contraceptives

Estrogens may decrease the hepatic metabolism of certain corticosteroids, thereby increasing their effect.

7.13 Nonsteroidal Anti-Inflammatory Drugs (NSAIDs) Including Aspirin and Salicylates

Concomitant use of aspirin or other nonsteroidal anti-inflammatory drugs and corticosteroids increases the risk of gastrointestinal side effects. Aspirin should be used cautiously in conjunction with corticosteroids in hypoprothrombinemia. The clearance of salicylates may be increased with concurrent use of corticosteroids; this could lead to decreased salicylate serum levels or increase the risk of salicylate toxicity when corticosteroid is withdrawn.

7.14 Potassium-Depleting Agents (e.g., Diuretics, Amphotericin B)

When corticosteroids are administered concomitantly with potassium-depleting agents, patients should be observed closely for development of hypokalemia.

7.15 Skin Tests

Corticosteroids may suppress reactions to skin tests.

7.16 Toxoids and Live or Attenuated Vaccines

Patients on corticosteroid therapy may exhibit a diminished response to toxoids and live or inactivated vaccines due to inhibition of antibody response. Corticosteroids may also potentiate the replication of some organisms contained in live attenuated vaccines. Routine administration of vaccines or toxoids should be deferred until corticosteroid therapy is discontinued if possible [ see Warnings and Precautions (5.8)].

8 USE IN SPECIFIC POPULATIONS

8.1 Pregnancy

Risk Summary

Based on findings from human and animal studies, corticosteroids, including prednisone delayed-release tablets, can cause fetal harm when administered to a pregnant woman (see Data) [see Warnings and Precautions (5.10)]. Published epidemiological studies suggest a small but inconsistent increased risk of orofacial clefts with use of corticosteroids during the first trimester. Intrauterine growth restriction and decreased birth weight have also been reported with maternal use of corticosteroids during pregnancy; however, the underlying maternal condition may also contribute to these risks (see Clinical Considerations). Published animal studies show prednisolone to be teratogenic in rats, rabbits, hamsters, and mice with increased incidence of cleft palate in offspring (see Data). Advise a pregnant woman about the potential harm to a fetus.

The estimated background risk of major birth defects and miscarriage for the indicated populations is unknown. All pregnancies have a background risk of birth defect, loss or other adverse outcomes. In the US general population, the estimated background risk of major birth defects and miscarriage in clinical recognized pregnancies is 2% to 4% and 15% to 20%, respectively.

Clinical Considerations

Fetal/Neonatal Adverse Reactions

Infants born to pregnant women who have received corticosteroids should be carefully monitored for signs and symptoms of hypoadrenalism [see Warnings and Precautions (5.1)]

Data

Human Data

Published epidemiological studies on the association between prednisolone and fetal outcomes have reported inconsistent findings and have important methodological limitations. Multiple cohort and case-controlled studies in humans suggest that maternal corticosteroid use during the first trimester increases the incidence of cleft lip with or without cleft palate from about 1/1000 infants to 3-5/1000 infants; however, a risk for orofacial clefts has not been observed in all studies. Methodological limitations of these studies include non-randomized design, retrospective data collection, and the inability to control for confounders such as underlying maternal disease and use of concomitant medications.

Two prospective case control studies showed decreased birth weight in infants exposed to maternal corticosteroids in utero. In humans, the risk of decreased birth weight appears to be dose related and may be minimized by administering lower corticosteroid doses. It is likely that underlying maternal conditions contribute to intrauterine growth restriction and decreased birth weight, but it is unclear to what extent these maternal conditions contribute to the increased risk of orofacial clefts.

Animal Data

Prednisolone, the active metabolite of prednisone, administered during the period of organogenesis, has been shown to be teratogenic in rats, rabbits, hamsters, and mice with increased incidence of cleft palate in offspring. In teratogenicity studies, cleft palate along with elevation of fetal lethality (or increase in resorptions) and reductions in fetal body weight were seen in rats at maternal doses of 30 mg/kg (equivalent to 290 mg in a 60 kg individual based on mg/m^2body surface comparison) and higher. Cleft palate was observed in mice at a maternal dose of 20 mg/kg (equivalent to 100 mg in a 60 kg individual based on mg/m^2comparison). Additionally, constriction of the ductus arteriosus has been observed in fetuses of pregnant rats exposed to prednisolone. Prednisone delayed-release tablets was not formally evaluated in animal reproduction studies.

8.2 Lactation

Risk Summary

Prednisolone has been found to be present in human milk following administration to lactating women. Published reports suggest infant daily doses are estimated to be less than 1% of the maternal daily dose. No adverse effects in the breastfed infant have been reported following maternal exposure of prednisolone during breastfeeding. There are no available data on the effects of prednisolone on milk production. High doses of corticosteroids administered to lactating women for long periods could potentially produce problems in the breastfed infant including growth and development and interfere with endogenous corticosteroid production (see Clinical Considerations) [see Use in Specific Populations (8.4)]. The developmental and health benefits of breastfeeding should be considered along with the mother's clinical need for prednisone delayed-release tablets and any potential adverse effects on the breastfed child from prednisone delayed-release tablets or from the mother's underlying condition.

Clinical Considerations

In order to minimize exposure, the lowest dose should be prescribed to lactating women to achieve the desired clinical effect.

Data

Human Data

Reports suggest that prednisolone concentrations in human milk are 5% to 25% of maternal serum levels, and that total infant daily doses are small, about 0.14% of the maternal daily dose.

8.4 Pediatric Use

The efficacy and safety of prednisone in the pediatric population are based on the well-established course of effect of corticosteroids which is similar in pediatric and adult populations. Published studies provide evidence of efficacy and safety in pediatric patients for the treatment of nephrotic syndrome (> 2 years of age), and aggressive lymphomas and leukemias (> 1 month of age). However, some of these conclusions and other indications for pediatric use of corticosteroid, e.g., severe asthma and wheezing, are based on adequate and well-controlled trials conducted in adults, on the premises that the course of the diseases and their pathophysiology are considered to be substantially similar in both populations. The adverse effects of prednisone in pediatric patients are similar to those in adults [ see Adverse Reactions (6)]. Like adults, pediatric patients should be carefully observed with frequent measurements of blood pressure, weight, height, intraocular pressure, and clinical evaluation for the presence of infection, psychosocial disturbances, thromboembolism, peptic ulcers, cataracts, and osteoporosis.

Children who are treated with corticosteroids by any route, including systemically administered corticosteroids, may experience a decrease in their growth velocity. This negative impact of corticosteroids on growth has been observed at low systemic doses and in the absence of laboratory evidence of HPA axis suppression (i.e., cosyntropin stimulation and basal cortisol levels). Growth velocity may therefore be a more sensitive indicator of systemic corticosteroid exposure in children than some commonly used tests of HPA axis function. The linear growth of children treated with corticosteroids by any route should be monitored, and the potential growth effects of prolonged treatment should be weighed against clinical benefits obtained and the availability of other treatment alternatives. In order to minimize the potential growth effects of corticosteroids, children should be titrated to the lowest effective dose [ see Warnings and Precautions (5.9)].

8.5 Geriatric Use

No overall differences in safety or effectiveness were observed between elderly subjects and younger subjects, and other reported clinical experience with prednisone has not identified differences in responses between the elderly and younger patients. However, the incidence of corticosteroid-induced side effects may be increased in geriatric patients and are dose-related. Osteoporosis is the most frequently encountered complication, which occurs at a higher incidence rate in corticosteroid-treated geriatric patients as compared to younger populations and in age-matched controls. Losses of bone mineral density appear to be greatest early on in the course of treatment and may recover over time after steroid withdrawal or use of lower doses (i.e., ≤ 5 mg/day). Prednisone doses of 7.5 mg/day or higher have been associated with an increased relative risk of both vertebral and nonvertebral fractures, even in the presence of higher bone density compared to patients with involution osteoporosis. Routine screening of geriatric patients, including regular assessments of bone mineral density and institution of fracture prevention strategies, along with regular review of prednisone indication should be undertaken to minimize complications and keep the prednisolone dose at the lowest acceptable level. Co-administration of certain bisphosphonates have been shown to retard the rate of bone loss in corticosteroid-treated males and postmenopausal females, and these agents are recommended in the prevention and treatment of corticosteroid-induced osteoporosis [ see Warnings and Precautions (5.6)].

It has been reported that equivalent weight-based doses yield higher total and unbound prednisolone plasma concentrations and reduced renal and non-renal clearance in elderly patients compared to younger populations. Dose selection for an elderly patient should be cautious, usually starting at the low end of the dosing range, reflecting the greater frequency of decreased hepatic, renal, or cardiac function, and of concomitant disease or other drug therapy.

This drug is known to be substantially excreted by the kidney, and the risk of toxic reactions to this drug may be greater in patients with impaired renal function. Because elderly patients are more likely to have decreased renal function, care should be taken in dose selection, and it may be useful to monitor renal function.

10 OVERDOSAGE

The effects of accidental ingestion of large quantities of prednisone over a very short period of time have not been reported, but prolonged use of the drug can produce mental symptoms, moon face, abnormal fat deposits, fluid retention, excessive appetite, weight gain, hypertrichosis, acne, striae, ecchymosis, increased sweating, pigmentation, dry scaly skin, thinning scalp hair, increased blood pressure, tachycardia, thrombophlebitis, decreased resistance to infection, negative nitrogen balance with delayed bone and wound healing, headache, weakness, menstrual disorders, accentuated menopausal symptoms, neuropathy, fractures, osteoporosis, peptic ulcer, decreased glucose tolerance, hypokalemia, and adrenal insufficiency. Hepatomegaly and abdominal distention have been observed in children.

Treatment of acute overdosage is by immediate gastric lavage or emesis followed by supportive and symptomatic therapy. For chronic overdosage in the face of severe disease requiring continuous steroid therapy the dosage of prednisone may be reduced only temporarily, or alternate day treatment may be introduced.

11 DESCRIPTION

The active ingredient in prednisone delayed-release tablet is prednisone (a corticosteroid). Corticosteroids are adrenocortical steroids, both naturally occurring and synthetic. The molecular formula for prednisone is C21H26O5. The chemical name for prednisone is 17,21-dihydroxypregna-1,4-diene-3,11,20-trione, and the structural formula is:

Prednisone, USP is a white to practically white crystalline powder and has a molecular weight of 358.44 g/mol. Prednisone, USP is practically insoluble in water, slightly soluble in ethanol (96 per cent) and in methylene chloride.

Prednisone delayed-release tablet is a delayed-release prednisone tablet. It consists of a prednisone-containing core tablet in an inactive shell, which delays the onset of in vitro drug dissolution by approximately 4 hours. Each tablet contains 1 mg, or 2 mg of prednisone, USP with the following inactive ingredients: dibasic calcium phosphate dihydrate, colloidal silicon dioxide, croscarmellose sodium, glycerol dibehenate, lactose monohydrate, magnesium stearate, povidone, yellow ferric oxide and red ferric oxide.

Each prednisone delayed-release tablet contains 30 mg of phosphorous.

Each prednisone delayed-release tablet contains less than 5 mg of sodium.

12 CLINICAL PHARMACOLOGY

12.1 Mechanism of Action

Naturally occurring corticosteroids (hydrocortisone and cortisone), which also have salt-retaining properties, are used as replacement therapy in adrenocortical deficiency states. Their synthetic analogs, such as prednisone, are primarily used for their potent anti-inflammatory effects in disorders of many organ systems.

Corticosteroids, such as prednisone, cause profound and varied metabolic effects. In addition, they modify the body's immune responses to diverse stimuli.

Prednisone is a synthetic adrenocortical steroid drug with predominantly corticosteroid properties. Some of these properties reproduce the physiological actions of endogenous glucocorticosteroids, but others do not necessarily reflect any of the adrenal hormones' normal functions; they are seen only after administration of large therapeutic doses of the drug. The pharmacological effects of prednisone which are due to its corticosteroid properties include: promotion of gluconeogenesis; increased deposition of glycogen in the liver; inhibition of the utilization of glucose; anti-insulin activity; increased catabolism of protein; increased lipolysis; stimulation of fat synthesis and storage; increased glomerular filtration rate and resulting increase in urinary excretion of urate (creatinine excretion remains unchanged); and increased calcium excretion.

Depressed production of eosinophils and lymphocytes occurs, but erythropoiesis and production of polymorphonuclear leukocytes are stimulated. Inflammatory processes (edema, fibrin deposition, capillary dilatation, migration of leukocytes and phagocytosis) and the later stages of wound healing (capillary proliferation, deposition of collagen, cicatrization) are inhibited.

Prednisone can stimulate secretion of various components of gastric juice. Suppression of the production of corticotropin may lead to suppression of endogenous corticosteroids. Prednisone has slight mineralocorticoid activity, whereby entry of sodium into cells and loss of intracellular potassium is stimulated. This is particularly evident in the kidney, where rapid ion exchange leads to sodium retention and hypertension.

12.3 Pharmacokinetics

The pharmacokinetic profile of prednisone delayed-release tablets has an approximately 4-hour lag time from that of immediate-release prednisone formulations. While the pharmacokinetic profile of prednisone delayed-release tablets when given with food differs in terms of lag time from IR prednisone, its absorption, distribution, and elimination processes are comparable.

Absorption

Prednisone is released from prednisone delayed-release tablets when taken with food approximately 4 hours after oral ingestion. This causes a delay in the time until peak plasma concentrations (Tmax) are achieved. Median Tmaxof prednisone delayed-release tablets in 27 healthy male subjects was 6.0 - 6.5 hours compared to 2.0 hours for an immediate-release (IR) formulation. Subsequently, prednisone was absorbed at the same rate as the IR formulation. Peak plasma concentrations (Cmax) and exposure, as indicated by AUC0-lastand AUC0-∞, were comparable for both prednisone IR and prednisone delayed-release tablets administered 2.5 hours after a light meal or with normal meal (Figure 1).

Figure 1. Mean Plasma Levels of Prednisone After a Single Dose of 5 mg Prednisone Administered as a 5 mg Prednisone Delayed-Release Tablet or a 5 mg Immediate-Release (IR) Tablet

A: 5 mg IR tablet under fasting conditions, administered at 2 am, B: 5 mg prednisone delayed-release tablets, administered 2.5 hours after a light evening meal, and C: 5 mg prednisone delayed-release tablets administered immediately after dinner

In a study with 24 healthy subjects, oral absorption of prednisone from prednisone delayed-release tablets was significantly affected by the intake of food. Under standard fasting conditions, both the maximum plasma concentration (Cmax) and the bioavailability of prednisone delayed-release tablets were significantly lower than under fed conditions, shortly after intake of a high fat meal.

Prednisone delayed-release tablets at dose levels of 1 mg, 2 mg, and 5 mg showed dose-proportionality in terms of peak and systemic exposure (Cmax, AUC0-∞, and AUC0-last) for the parent drug prednisone as well as for the active metabolite prednisolone.

Metabolism

Prednisone is completely converted to the active metabolite prednisolone, which is further metabolized mainly in the liver and excreted in the urine as sulfate and glucuronide conjugates. The exposure of prednisolone is 4-6 fold higher than that of prednisone.

Excretion

The terminal half-life of both prednisone and prednisolone from the administration of prednisone delayed-release tablets was 2-3 hours, which is comparable to that from the IR formulation.

Special Populations

The effects of gender, age, renal impairment, and hepatic impairment on the pharmacokinetics of prednisone or prednisolone after administration of prednisone delayed-release tablets have not been evaluated.

13 NONCLINICAL TOXICOLOGY

13.1 Carcinogenesis, Mutagenesis, Impairment of Fertility

Prednisone was not formally evaluated in carcinogenicity studies. Review of the published literature identified carcinogenicity studies of prednisolone, the active metabolite of prednisone, at doses which were less than the typical clinical doses. In a 2-year study, male Sprague-Dawley rats administered prednisolone in drinking water at a dose of 368 mcg/kg/day (equivalent to 3.5 mg/day in a 60-kg individual based on a mg/m^2body surface area comparison) developed increased incidences of hepatic adenomas. Lower doses were not studied, and therefore, a no effect level could not be identified. In an 18-month study, intermittent oral gavage administration of prednisolone did not induce tumors in female Sprague-Dawley rats when given 1, 2, 4.5, or 9 times per month at 3 mg/kg prednisone (equivalent to 29 mg in a 60-kg individual based on a mg/m^2body surface area comparison).

Prednisone was not formally evaluated for genotoxicity. However, in published studies prednisolone was not mutagenic with or without metabolic activation in the Ames bacterial reverse mutation assay using Salmonella typhimuriumand Escherichia coli, or in a mammalian cell gene mutation assay using mouse lymphoma L5178Y cells, according to current evaluation standards. In a published chromosomal aberration study in Chinese Hamster Lung (CHL) cells, a slight increase was seen in the incidence of structural chromosomal aberrations with metabolic activation at the highest concentration tested, however, the effect appears to be equivocal. Prednisolone was not genotoxic in an in vivomicronucleus assay in the mouse, though the study design did not meet current criteria.

Prednisone was not formally evaluated in fertility studies. Corticosteroids have been shown to impair fertility in male rats. Menstrual irregularities have been described with clinical use [ see Adverse Reactions (6)].

14 CLINICAL STUDIES

The efficacy of prednisone delayed-release tablets in the treatment of rheumatoid arthritis was assessed in one multicenter, double-blind, placebo-controlled, randomized, 12-week trial in patients ≥18 years with active rheumatoid arthritis diagnosed according to American College of Rheumatology (ACR) criteria. Patients were enrolled who were not currently treated with corticosteroids but had received non-biologic DMARD therapy for at least 6 months before receipt of study medication, and had an incomplete response to DMARD therapy alone. Patients were randomized in a 2:1 ratio to treatment with prednisone delayed-release tablets 5 mg (n=231) or placebo (n=119) administered at 10 pm. A total of 350 patients were enrolled and ranged in age from 27 to 80 years (median age 57 years) with 84% females. Race was distributed as follows: 98% Caucasian, 1% African-American, and <1% Asian.

The percentage of patients with improvement in rheumatoid arthritis at 12 weeks using ACR response criteria (ACR20) was assessed as the primary endpoint, and ACR20, ACR50 and ACR70 responses for patients treated with prednisone delayed-release tablets 5 mg versus placebo are shown in Table 1. The relative efficacy of prednisone delayed-release tablets compared to immediate-release prednisone has not been established.

Table 1. ACR Responses (Percentage of Patients)
ACR Response at 12 Weeks | Prednisone delayed-release tablets 5 mg | Placebo | Prednisone delayed-release tablets 5 mg – Placebo (95% CI)
ACR Response at 12 Weeks | N = 231 | N = 119
ACR20 | 47% | 29% | 17% (7.2, 27.6)
ACR50 | 22% | 10% | 12% (4.4, 19.6)
ACR70 | 7% | 3% | 4% (0.1, 8.7)
All missing values were imputed as non-responders.

The results of the components of the ACR response criteria are shown in Table 2.

Table 2. Components of ACR Response
Parameter | Prednisone delayed-release tablets 5 mg + DMARD N = 231 |  | Placebo + DMARD N = 119
Parameter | Baseline | Week 12 | Baseline | Week 12
Tender joint counta | 12.6 (6.2) | 7.9 (6.8) | 12.5 (5.9) | 9.8 (6.7)
Swollen joint counta | 8.4 (4.4) | 4.8 (4.8) | 8.6 (4.7) | 6.1 (5.4)
Patient assessment of painb | 55.3 (21.9) | 33.0 (24.5) | 50.5 (23.3) | 39.6 (24.7)
Patient global assessmentc | 57.4 (20.1) | 36.2 (24.5) | 50.9 (20.9) | 43.0 (22.4)
Physician global assessmentc | 55.2 (16.1) | 31.9 (19.7) | 54.1 (17.4) | 40.4 (21.8)
Disability index (HAQ-DI)d | 1.3 (0.6) | 1.1 (0.6) | 1.3 (0.6) | 1.2 (0.6)
ESR (mm/hr) | 33.0 (16.6) | 25.2 (16.8) | 32.9 (20.0) | 26.5 (19.7)
CRP (mg/dL) | 9.3 (13.2) | 7.5 (10.7) | 11.8 (18.0) | 9.7 (12.1)
Mean (SD) is presented. Baseline values were carried forward for patients with missing data at Week 12.

a 28-joint count

b Patient assessment of arthritis pain. Visual analog scale: 0 = no pain, 100 = very intensive pain

cPatient or physician global assessment of disease activity. Visual analog scale: 0 = not active at all, 100 = extremely active

dHealth Assessment Questionnaire Disability Index; 0 = best, 3 = worst, measures the patient’s ability to perform the following: dress/groom, arise, eat, walk, reach, grip, maintain hygiene, and maintain daily activity

The percentage of patients achieving ACR20 responses by visit is shown in Figure 2.

Figure 2. ACR20 Response Over 12 Weeks

a The same patients may not have responded at each time point.

The percent change from baseline in the duration of morning stiffness at 12 weeks was assessed as a prespecified secondary endpoint. Patients treated with prednisone delayed-release tablets had a median decrease in the duration of morning stiffness of 55% compared to 33% in placebo-treated patients (20% estimated median difference between treatment groups with 95% confidence interval [7, 32]). This corresponds to a median duration of morning stiffness of 46 minutes in the prednisone delayed-release tablets group and 85 minutes in the placebo group.

16 HOW SUPPLIED/STORAGE AND HANDLING

Prednisone delayed-release tablets (1 mg prednisone) are white to off-white colored, round, unscored, delayed release tablet, debossed with "1" on one side and plain on other side, mottled appearance, free from physical defects.

NDC Number | Size
74157-010-30 | Bottle of 30 tablets

Prednisone delayed-release tablets (2 mg prednisone) are light peach to peach colored, round, unscored, delayed release tablet, debossed with "2" on one side and plain on other side, mottled appearance, free from physical defects.

NDC Number | Size
74157-019-30 | Bottle of 30 tablet

STORAGE AND HANDLING

Store at 20°C to 25°C (68°F to 77°F); excursions permitted to 15°C to 30°C (59°F to 86°F) [See USP Controlled Room Temperature].

Protect prednisone delayed-release tablets from light and moisture.

Dispense in a tight, light-resistant container as defined in the USP using a child-resistant closure.

17 PATIENT COUNSELING INFORMATION

Patients should be informed of the following information before initiating therapy with prednisone delayed-release tablets and periodically during the course of ongoing therapy.

- Patients should be warned not to discontinue the use of prednisone delayed-release tablets abruptly or without medical supervision, to advise any medical attendants that they are taking it, and to seek medical advice at once should they develop fever or other signs of infection. Patients should be told to take prednisone delayed-release tablets exactly as prescribed, follow the instructions on the prescription label, and not stop taking prednisone delayed-release tablets without first checking with their healthcare providers, as there may be a need for gradual dose reduction.
- Patients should discuss with their physician if they have had recent or ongoing infections or if they have recently received a vaccine.
- Persons who are on immunosuppressant doses of corticosteroids should be warned to avoid exposure to chickenpox or measles. Patients should also be advised that if they are exposed, medical advice should be sought without delay.
- There are a number of medicines that can interact with prednisone delayed-release tablets. Patients should inform their healthcare provider of all the medicines they are taking, including over-the-counter and prescription medicines (such as phenytoin, diuretics, digitalis or digoxin, rifampin, amphotericin B, cyclosporine, insulin or diabetes medicines, ketoconazole, estrogens including birth control pills and hormone replacement therapy, blood thinners such as warfarin, aspirin or other NSAIDs, barbiturates), dietary supplements, and herbal products. If patients are taking any of these drugs, alternate therapy, dosage adjustment, and/or special test may be needed during the treatment.
- For missed doses, patients should be told to take the missed dose as soon as they remember. If it is almost time for the next dose, the missed dose should be skipped and the medicine taken at the next regularly schedule time. Patients should not take an extra dose to make up for the missed dose.
- Patients should be told to take prednisone delayed-release tablets with food. Patients should be advised not to break, divide, or chew prednisone delayed-release tablets.
- Patients should be advised of common adverse reactions that could occur with prednisone delayed-release tablets use to include fluid retention, alteration in glucose tolerance, elevation in blood pressure, behavioral and mood changes, increased appetite and weight gain.
- Advise pregnant women and females of reproductive potential of the potential risk to a fetus. Advise females to inform their healthcare provider of a known or suspected pregnancy [see Warnings and Precautions (5.10)and Use in Specific Populations (8.1)].

Manufactured For:

INA Pharmaceutics Inc
Fairmont, WV 26554
Product of Spain

Issued: 11/2025

PACKAGE LABEL

NDC 74157-010-30

predniSONE Delayed-release Tablets

1 mg
30 Tablets

Swallow whole. Do not crush,
divide, or chew tablets.

Rx Only

NDC 74157-019-30

predniSONE Delayed-release Tablets

2 mg
30 Tablets

Swallow whole. Do not crush,
divide, or chew tablets.

Rx Only